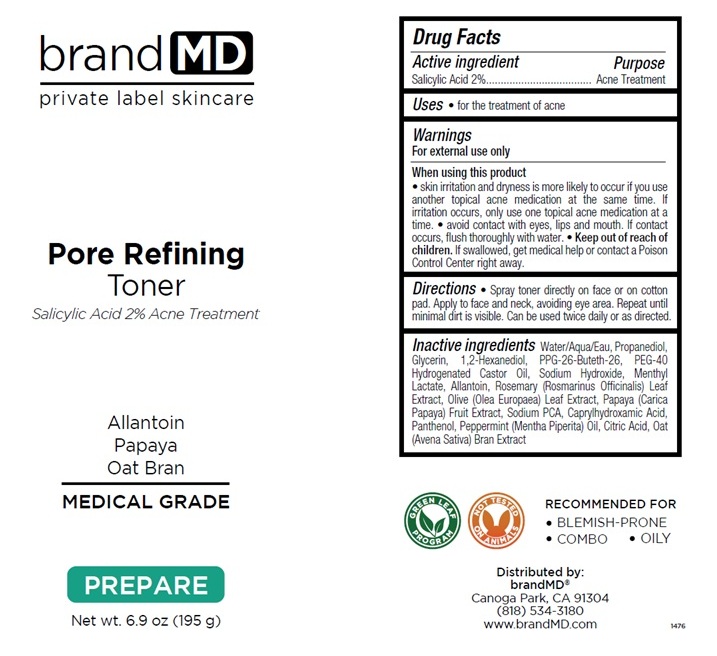 DRUG LABEL: Pore Refining Toner
NDC: 72957-013 | Form: LIQUID
Manufacturer: Private Label Skin Care
Category: otc | Type: HUMAN OTC DRUG LABEL
Date: 20250227

ACTIVE INGREDIENTS: SALICYLIC ACID 2 g/100 g
INACTIVE INGREDIENTS: WATER; PROPANEDIOL; GLYCERIN; 1,2-HEXANEDIOL; PPG-26-BUTETH-26; POLYOXYL 40 HYDROGENATED CASTOR OIL; SODIUM HYDROXIDE; MENTHYL LACTATE, (-)-; ALLANTOIN; ROSEMARY; OLEA EUROPAEA LEAF; PAPAYA; SODIUM PYRROLIDONE CARBOXYLATE; CAPRYLHYDROXAMIC ACID; PANTHENOL; PEPPERMINT OIL; CITRIC ACID MONOHYDRATE; OAT BRAN

Pore Refining Toner

Active ingredient

Salicylic Acid 2%

Purpose

Acne Treatment

Uses

• for the treatment of acne

Warnings

For external use only

When using this product

• skin irritation and dryness is more likely to occur if you use another topical acne medication at the same time. If irritation occurs, only use one topical acne medication at a time. • avoid contact with eyes, lips and mouth. If contact occurs, flush thoroughly with water.

• Keep out of reach of children. If swallowed, get medical help or contact a Poison Control Center right away.

Directions

• Spray toner directly on face or on cotton pad. Apply to face and neck, avoiding eye area. Repeat until minimal dirt is visible. Can be used twice daily or as directed.

Inactive ingredients

Water/Aqua/Eau, Propanediol, Glycerin, 1,2-Hexanediol, PPG-26-Buteth-26, PEG-40 Hydrogenated Castor Oil, Sodium Hydroxide, Menthyl Lactate, Allantoin, Rosemary (Rosmarinus Officinalis) Leaf Extract, Olive (Olea Europaea) Leaf Extract, Papaya (Carica Papaya) Fruit Extract, Sodium PCA, Caprylhydroxamic Acid, Panthenol, Peppermint (Mentha Piperita) Oil, Citric Acid, Oat (Avena Sativa) Bran Extract

brand MD

Allantoin
Papaya
Oat Bran

MEDICAL GRADE

PREPARE

RECOMMENDED FOR

• BLEMISH-PRONE
• COMBO • OILY

GREEN LEAF PROGRAM

NOT TESTED ON ANIMALS

Distributed by:
brandMD®
Canoga Park, CA 91304
(818) 534-3180
www.brandMD.com